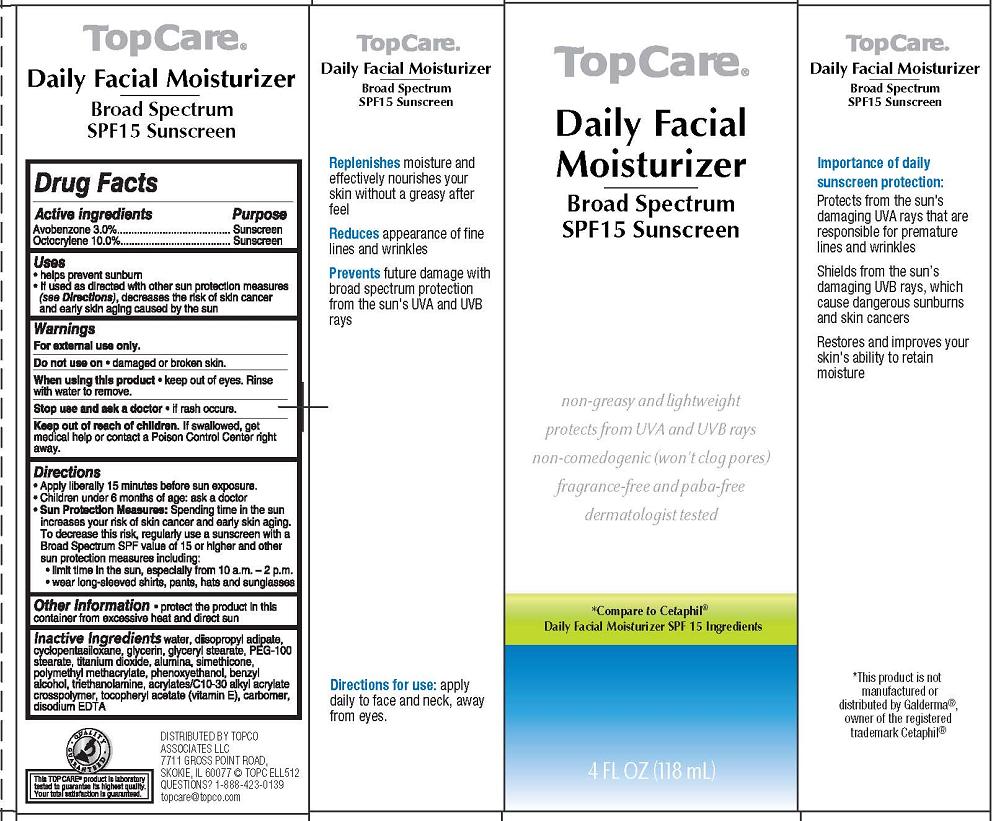 DRUG LABEL: Topcare Daily Facial
NDC: 36800-326 | Form: CREAM
Manufacturer: Topco Associates LLC
Category: otc | Type: HUMAN OTC DRUG LABEL
Date: 20120621

ACTIVE INGREDIENTS: AVOBENZONE 3 mL/100 mL; OCTOCRYLENE 10 mL/100 mL
INACTIVE INGREDIENTS: WATER; DIISOPROPYL ADIPATE; CYCLOMETHICONE 5; GLYCERIN; GLYCERYL MONOSTEARATE; PEG-100 STEARATE; TITANIUM DIOXIDE; ALUMINUM OXIDE; DIMETHICONE; POLY(METHYL ACRYLATE-CO-METHYL METHACRYLATE-CO-METHACRYLIC ACID 7:3:1; 280000 MW); PHENOXYETHANOL; BENZYL ALCOHOL; TROLAMINE; CARBOMER INTERPOLYMER TYPE A (55000 MPA.S); .ALPHA.-TOCOPHEROL ACETATE; CARBOMER HOMOPOLYMER TYPE A (ALLYL PENTAERYTHRITOL CROSSLINKED); EDETATE DISODIUM

TopCare® Daily Facial Moisturizer

Active ingredient

Avobenzone 3.0%

Octocrylene 10.0%

Purpose

Sunscreen

Uses

- helps prevent sunburn
- If used as directed with other sun protection measures (see Directions), decreases the risk of skin cancer and early skin aging caused by the sun

Warnings

For external use only.

Do not use on

- damaged or broken skin.

When using this product

- keep out of eyes. Rinse with water to remove.

Stop use and ask a doctor

- if rash occurs.

Keep Out of Reach of Children.

If swallowed, get medical help or contact a Poison Control Center right away.

Directions

- Apply liberally 15 minutes before sun exposure.
- Children under 6 months of age: ask a doctor
- Sun Protection Measures: Spending time in the sun increases your risk of skin cancer and early skin aging. To decrease this risk, regularly use a sunscreen with a Broad Spectrum SPF value of 15 or higher and other sun protection measures including:
  - limit time in the sun, especially from 10 a.m. - 2 p.m.
  - wear long-sleeved shirts, pants, hats and sunglasses

Other Information

- protect the product in this container from excessive heat and direct sun

Inactive Ingredients

water, disopropyl adipate, cyclopentasiloxane, glycerin, glyceryl stearate, PEG-100 stearate, titanium dioxide, alumina, simethicone, polymethyl methacrylate, phenoxyethanol, benzyl alcohol, triethanolamine, acrylates/C10-30 alkylacrylate crosspolymer, tocopheryl acetate (vitamin E), carbomer, disodium EDTA

Package/Label Principal Display Panel - Carton Label

TopCare®

Daily Facial Moisturizer Broad Spectrum SPF15 Sunscreen

non-greasy and lightweight

protects from UVA and UVB rays

non-comedogenic (won't clog pores)

fragrance-free and paba-free

dermatologist tested

*Compare to Cetaphil® Daily Facial Moisturizer SPF 15 Ingredients

4 FL OZ (118 mL)

DISTRIBUTED BY TOPCO
ASSOCIATES LLC
7711 GROSS POINT ROAD,
SKOKIE, IL 60077 © TOPC ELL512
QUESTIONS? 1-888-423-0139
topcare@topco.com

Carton Label